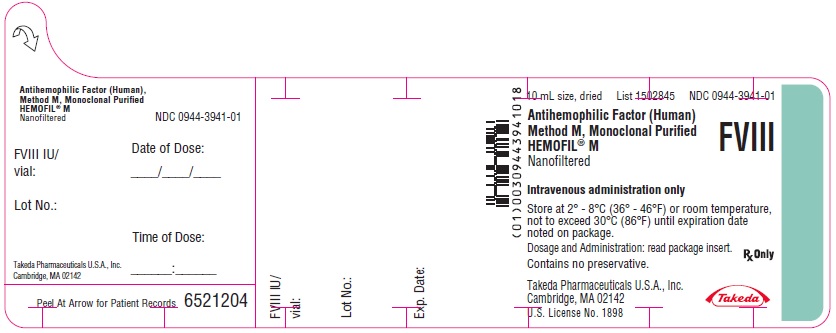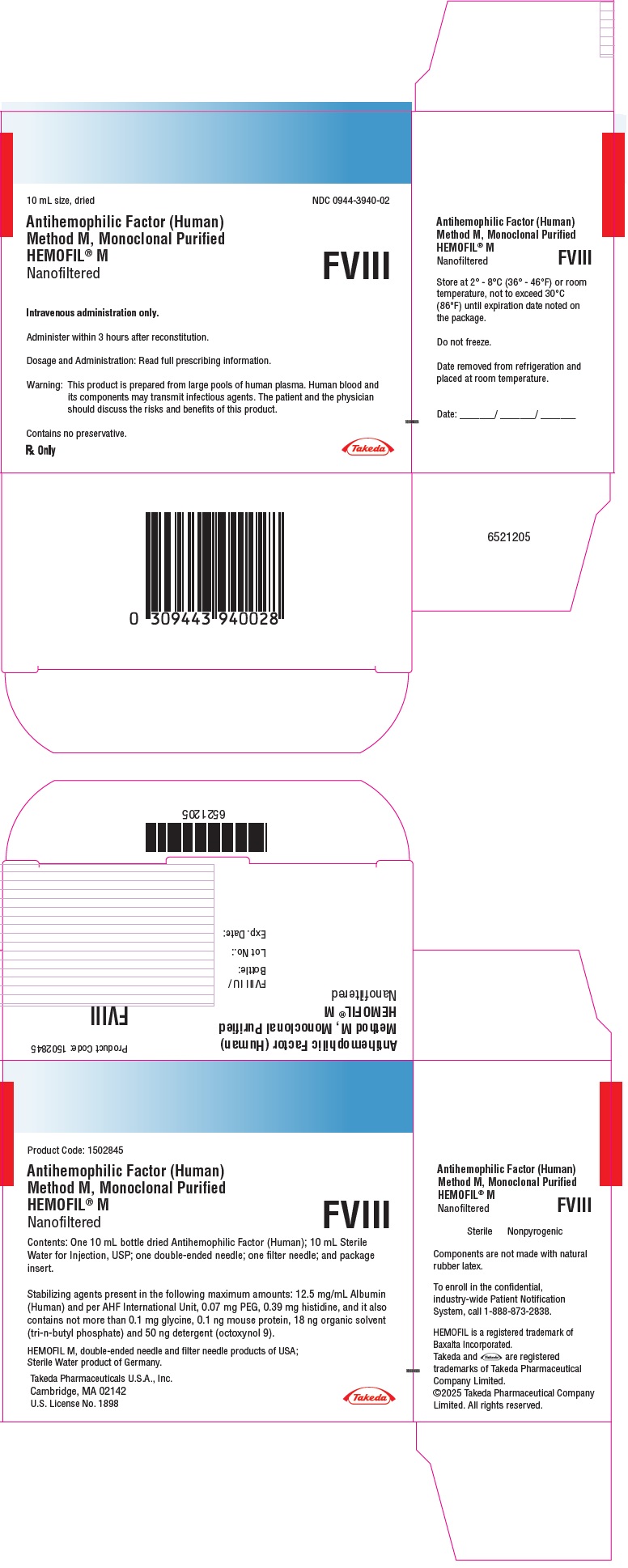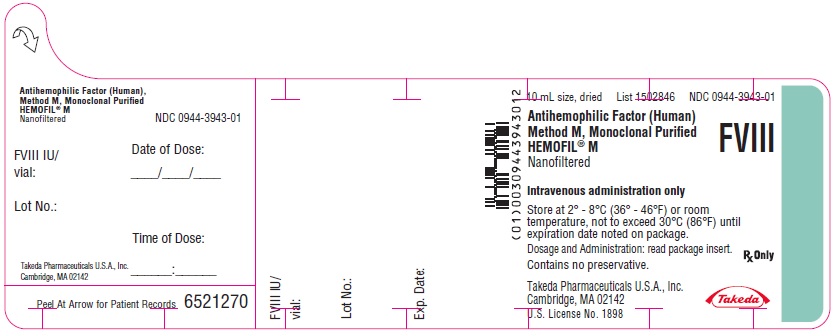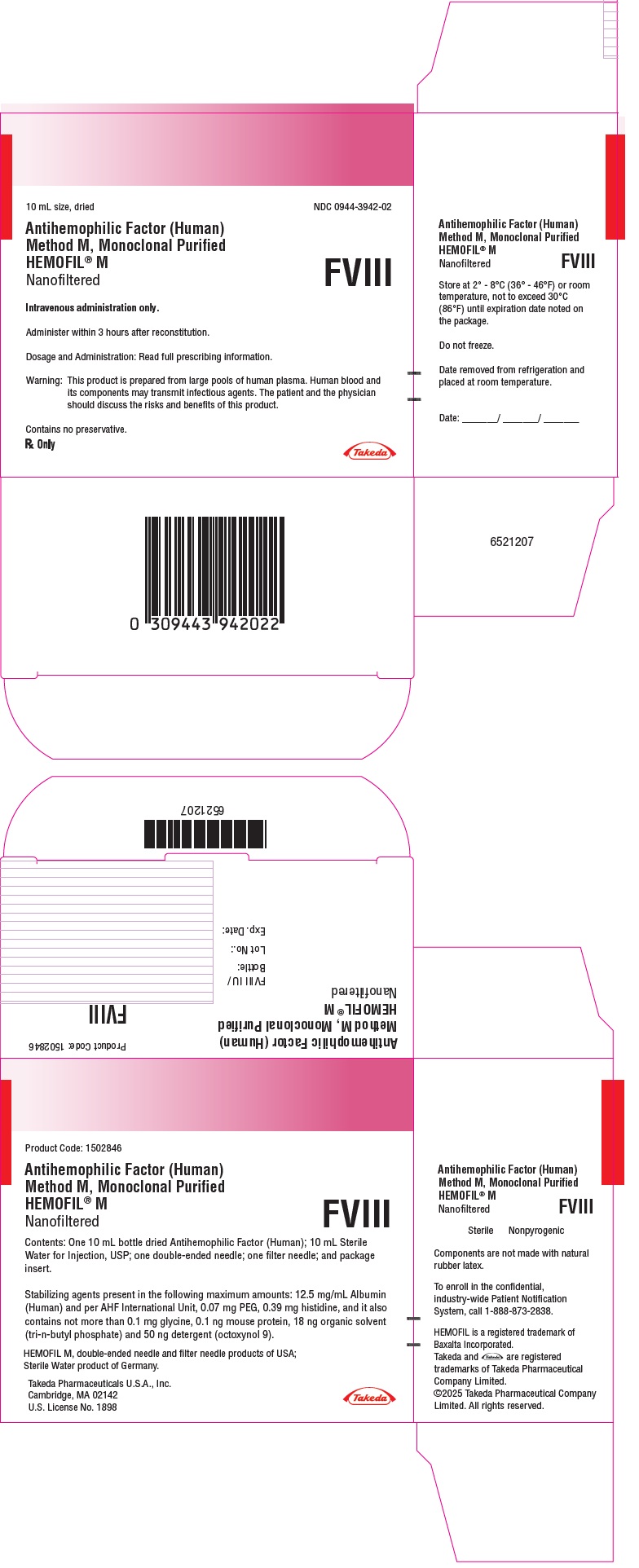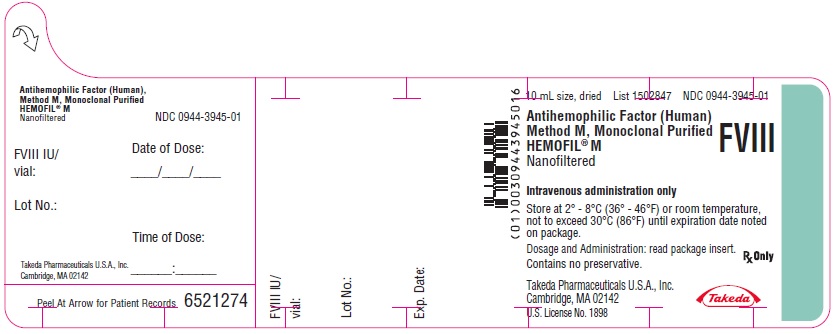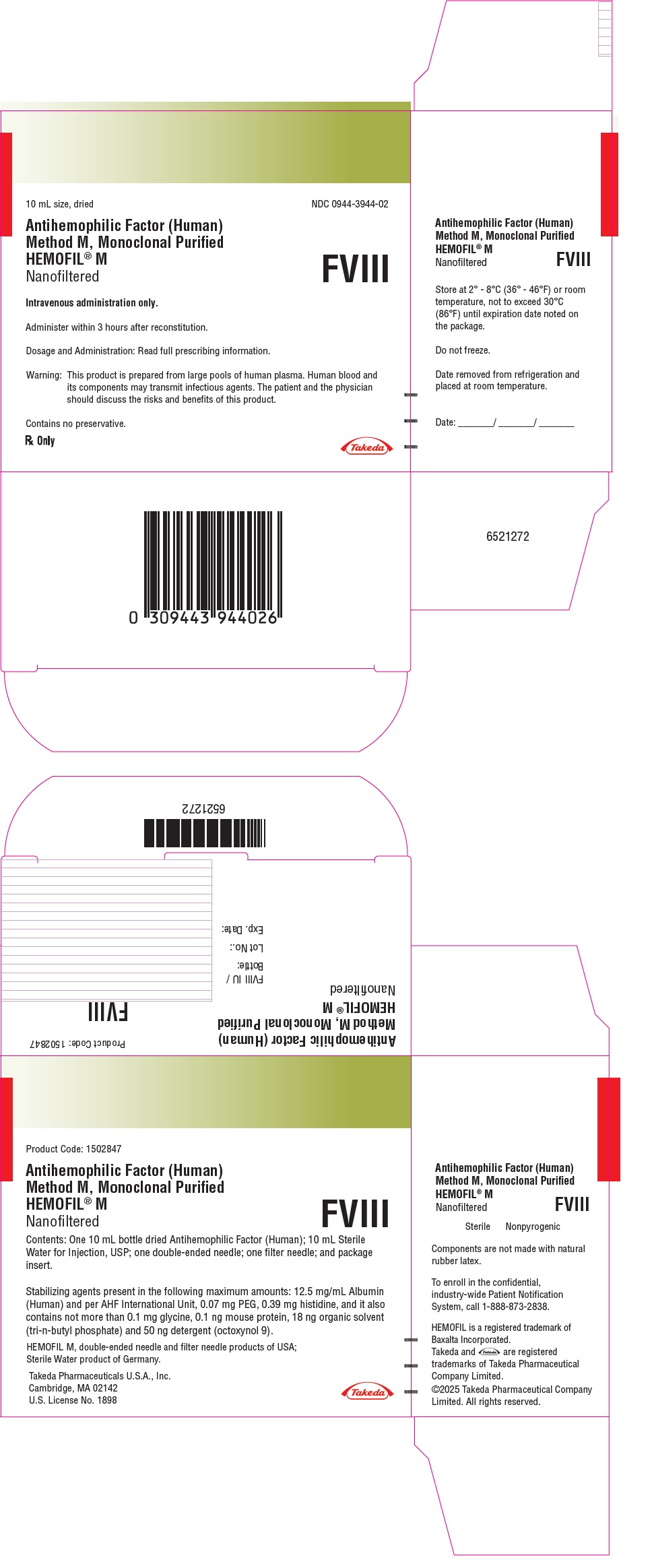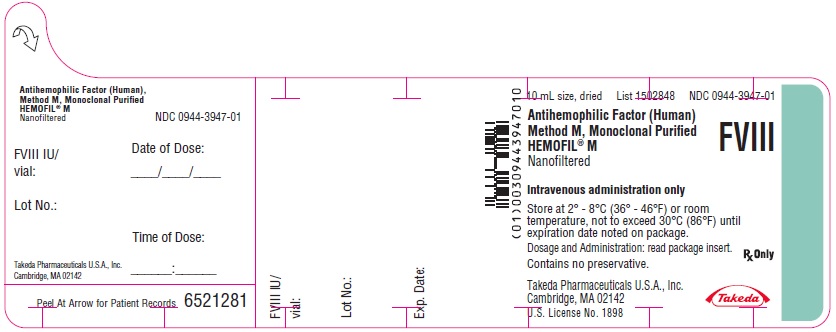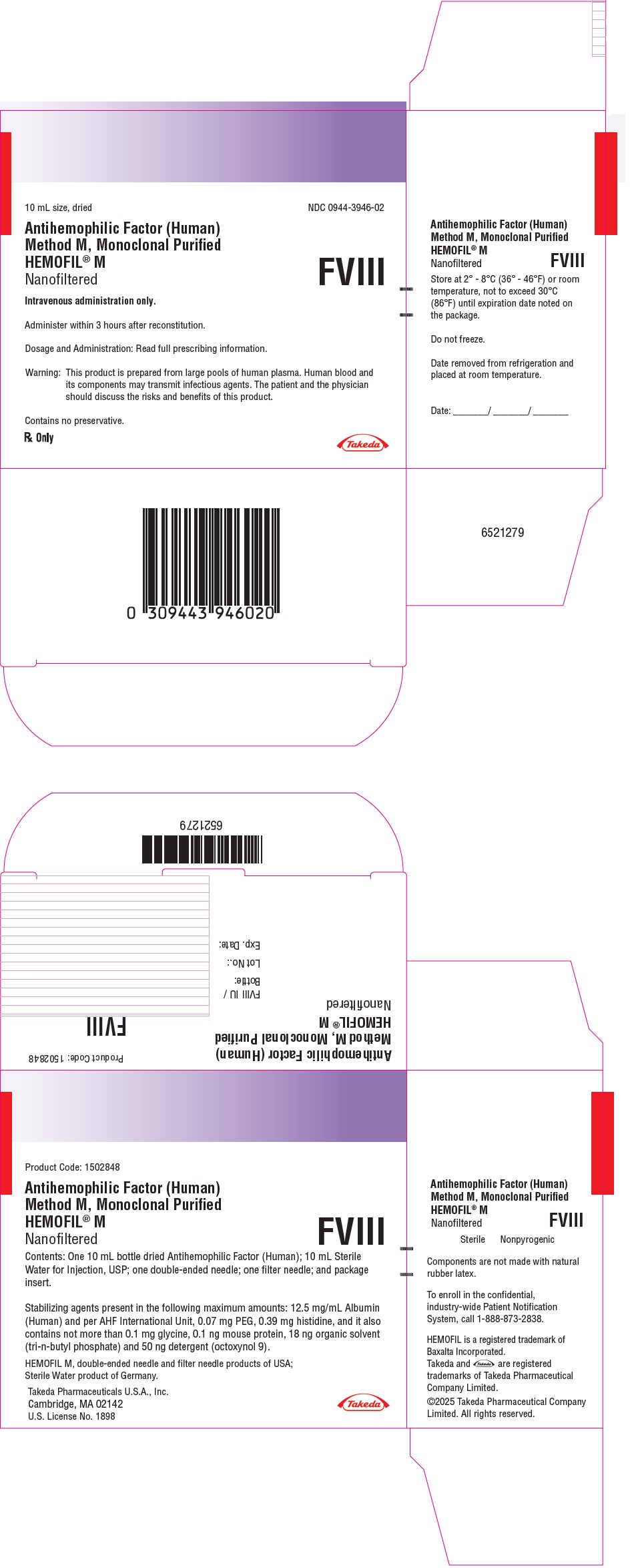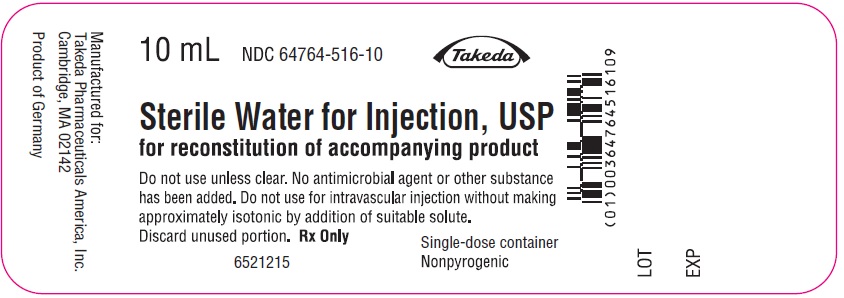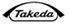 DRUG LABEL: HEMOFIL M
NDC: 0944-3940 | Form: KIT | Route: INTRAVENOUS
Manufacturer: Takeda Pharmaceuticals America, Inc.
Category: other | Type: PLASMA DERIVATIVE
Date: 20250306

ACTIVE INGREDIENTS: ANTIHEMOPHILIC FACTOR HUMAN 250 [iU]/10 mL
INACTIVE INGREDIENTS: ALBUMIN HUMAN; POLYETHYLENE GLYCOL 3350; HISTIDINE; WATER 10 mL/10 mL

HEMOFIL® M

Antihemophilic Factor (Human), Method M, Monoclonal Purified
Nanofiltered

DESCRIPTION

HEMOFIL M, Antihemophilic Factor (Human) (AHF), Method M, Monoclonal Purified, is a sterile, nonpyrogenic, dried preparation of antihemophilic factor (Factor VIII, Factor VIII:C, AHF) in concentrated form with a specific activity range of 2 to 22 AHF International Units/mg of total protein. HEMOFIL M contains a maximum of 12.5 mg/mL Albumin, and per AHF International Unit, 0.07 mg polyethylene glycol (3350), 0.39 mg histidine as stabilizing agents, not more than 0.1 mg glycine, 0.1 ng mouse protein, 18 ng organic solvent (tri-n-butyl phosphate) and 50 ng detergent (octoxynol 9). In the absence of the added Albumin (Human), the specific activity is approximately 2,000 AHF International Units/mg of protein [see Clinical Pharmacology].

HEMOFIL M is prepared by the Method M process from pooled human plasma by immunoaffinity chromatography utilizing a murine monoclonal antibody to Factor VIII:C, followed by an ion exchange chromatography step for further purification. Source material may be provided by other US licensed manufacturers. HEMOFIL M also includes an organic solvent (tri-n-butyl phosphate) and detergent (octoxynol 9) virus inactivation step designed to reduce the risk of transmission of hepatitis and other viral diseases. The process further includes a nanofiltration step between immunoaffinity chromatography and ion-exchange chromatography as an additional viral clearance step to further improve the viral safety margin of the final product.

Use of an organic solvent (tri-n-butyl phosphate; TNBP) in the manufacture of Antihemophilic Factor (Human) has little or no effect on AHF activity, while lipid enveloped viruses, such as hepatitis B and human immunodeficiency virus (HIV) would be inactivated.^1 The nanofiltration step integrated into the manufacture of AHF-M further enhances the safety margin with respect to adventitious viruses. Each bottle of HEMOFIL M is labeled with the AHF activity expressed in International Units (IU) per bottle. This potency assignment is referenced to the World Health Organization International Standard. The purity of HEMOFIL M has been thought to influence the difficulty of producing an accurate potency measurement. Experiments have shown that to achieve accurate activity levels, such a potency assay should be conducted using plastic test tubes and pipets as well as substrate containing normal levels of von Willebrand's Factor.

In vitro studies demonstrate that the HEMOFIL M manufacturing process provides for viral reduction. These reductions are achieved through a combination of process chemistry, partitioning and/or inactivation during solvent/detergent treatment, and immunoaffinity chromatography. Introduction of a nanofiltration step with the 0.1µm prefilter and the ASAHI Planova 20N nanofilter provides a virus removal capacity for human immunodeficiency virus, Type 1 (HIV-1), hepatitis A virus (HAV), bovine viral diarrhea virus (BVDV), pseudorabies virus (PRV), mice minute virus (MMV), and human parvovirus B19 (B19V) in the order of four (4) logs or higher. B19V removal data were obtained with a Polymerase Chain Reaction (PCR) assay not correlated to an infectivity assay.

Studies for nanofiltration and other process steps, summarized in Table 1, demonstrate virus clearance during the HEMOFIL M manufacturing process using HIV-1; BVDV, a generic model for lipid enveloped RNA viruses, such as hepatitis C virus (HCV); PRV, a model for lipid enveloped DNA viruses, such as hepatitis B virus (HBV); canine parvovirus (CPV), a model for non-lipid enveloped DNA viruses, such as B19V, HAV, and MMV.

Table 1 In Vitro Virus Clearance During the Manufacture of HEMOFIL M
Process Step Evaluated | Virus Clearance, log 10
Process Step Evaluated | Lipid-enveloped |  |  | Non-Lipid enveloped
Process Step Evaluated | HIV-1 | BVDV | PRV | HAV | CPV | MMV
Solvent/Detergent Treatment | >4.8 | >6.8 | >6.9 | NT [As Solvent/Detergent treatment does not inactivate non-lipid enveloped viruses.] | NT | NT
Immunoaffinity Chromatography | N.A. [Not Applicable for lipid enveloped viruses due to the presence of (virucidal) solvent/detergent reagents in the starting material.] | N.A. | N.A. | ≥4.5 | ≥3.9 | NT
Nanofiltration | >5.5 | >4.6 | >4.4 | >5.4 | NT | >5.0
Cumulative Total, log10 | >10.3 | >11.4 | >11.3 | >9.9 | ≥3.9 | >5.0
NT not tested

CLINICAL PHARMACOLOGY

Antihemophilic factor (AHF) is a protein found in normal plasma which is necessary for clot formation. The administration of HEMOFIL M provides an increase in plasma levels of AHF and can temporarily correct the coagulation defect of patients with hemophilia A (classical hemophilia). The half-life of HEMOFIL M administered to Factor VIII deficient patients has been shown to be 14.8 ± 3.0 hours.

INDICATIONS AND USAGE

HEMOFIL M is indicated in hemophilia A (classical hemophilia) for the prevention and control of hemorrhagic episodes.

HEMOFIL M is not indicated in von Willebrand's disease.

CONTRAINDICATIONS

HEMOFIL M is contraindicated in patients with a known hypersensitivity to the active substance, to excipients, or to mouse proteins.

WARNINGS

Hypersensitivity

Allergic-type hypersensitivity reactions, including anaphylaxis, have been reported with HEMOFIL M and have been manifested by bronchospasm, dyspnea, hypotension, chest pain, facial edema, urticaria, rash, flushing, pruritus, and nausea.

Neutralizing Antibodies

The development of neutralizing antibodies (inhibitors) to Factor VIII is a known complication of the treatment of patients with Hemophilia A. Inhibitors have predominantly been reported in previously untreated patients. The risk of developing inhibitors is correlated to the extent of exposure to Factor VIII, the risk being highest within the first 20 exposure days, and to other genetic and environmental factors. The risk for inhibitor development depends on a number of factors relating to the characteristics of the patient (e.g., type of the Factor VIII gene mutation, family history, ethnicity), which are believed to represent the most significant risk factors for inhibitor formation.

Transmission of Infectious Agents

Because HEMOFIL M is made from human blood, it may carry a risk of transmitting infectious agents, e.g., viruses, the variant Creutzfeldt-Jakob disease (vCJD) agent and, theoretically, the Creutzfeldt-Jakob disease (CJD) agent. This also applies to unknown or emerging viruses and other pathogens.

All infections thought by a physician possibly to have been transmitted by this product should be reported by the physician or other healthcare provider to Takeda Pharmaceuticals U.S.A., Inc. at 1-877-TAKEDA-7 (1-877-825-3327) or FDA at 1-800-FDA-1088 or www.fda.gov/medwatch. The physician should discuss the risks and benefits of this product with the patient.

Individuals who receive infusions of blood or plasma products may develop signs and/or symptoms of some viral infections, particularly non-A, non-B hepatitis. As indicated under Clinical Pharmacology, however, a group of such patients treated with HEMOFIL M did not demonstrate signs or symptoms of non-A, non-B hepatitis over observation periods ranging from three to nine months.

PRECAUTIONS

Identification of the clotting defect as a Factor VIII deficiency is essential before the administration of HEMOFIL M is initiated.

Factor VIII Inhibitors

Evaluate patients for the development of Factor VIII inhibitors if the expected plasma Factor VIII activity levels are not attained or if bleeding is not controlled with an appropriate dose.

No benefit may be expected from this product in treating other deficiencies.

Formation of Antibodies to Mouse Protein

HEMOFIL M contains trace amounts of mouse protein (less than 0.1 ng/AHF activity units). The possibility exists that patients treated with HEMOFIL M may develop hypersensitivity to the mouse proteins. There have been no cases of hypersensitivity to the mouse proteins reported.

Increase in Pulse Rate

Determine the pulse rate before and during administration of HEMOFIL M. Should a significant increase occur, reduce the rate of administration or temporarily halt the injection to allow the symptoms to disappear promptly.

Laboratory Tests

Perform appropriate laboratory tests on the patient's plasma at suitable intervals to ensure that adequate AHF levels have been reached and are maintained.

If the AHF content of the patient's plasma fails to reach expected levels or if bleeding is not controlled after apparently adequate dosage, the presence of inhibitor should be suspected. By appropriate laboratory procedures, the presence of inhibitor can be demonstrated and quantified in terms of AHF units neutralized by each mL of plasma or by the total estimated plasma volume.

If the inhibitor is at low levels (i.e., <10 Bethesda units per mL), after administration of sufficient AHF units to neutralize the inhibitor, additional AHF units will elicit the predicted response.

Pregnancy

Animal reproduction studies have not been conducted with HEMOFIL M. The safety of HEMOFIL M for use in pregnant women has not been established. It is not known whether HEMOFIL M can cause fetal harm when administered to a pregnant woman or can affect reproduction capacity. HEMOFIL M should be given to a pregnant woman only if clearly needed.

Nursing Mothers

The safety of HEMOFIL M for use in nursing mothers has not been established. It is not known whether this drug is excreted into human milk. Physicians should carefully consider the potential risks and benefits for each specific patient before prescribing HEMOFIL M. HEMOFIL M should be given to nursing mothers only if clinically indicated.

ADVERSE REACTIONS

Adverse Reactions from Clinical Trials

The adverse reactions presented in this section have been identified based on clinical trial experience with HEMOFIL M in patients previously treated with other Factor VIII concentrates or blood products (N = 74), and previously untreated patients (PUPs; N = 50).

Clinical Trial Adverse Reactions
System Organ Class (SOC) | Preferred MedDRA Term | Number of Cases; (Frequency; Percentage)
BLOOD AND LYMPHATIC; SYSTEM DISORDERS | Factor VIII inhibition | 3 (5.7%) [In a study that included 43 evaluable PUPs and 10 minimally treated patients (MTPs), i.e., patients with a single exposure to other Factor VIII concentrates or blood products, 3 of the total of 53 patients (5.7%) developed an inhibitor while on study.]
NERVOUS SYSTEM DISORDERS | Dizziness | 1 (0.8%)
NERVOUS SYSTEM DISORDERS | Headache | 1 (0.8%)
NERVOUS SYSTEM DISORDERS | Dysgeusia | 1 (0.8%)
GENERAL DISORDERS AND ADMINISTRATION SITE CONDITIONS | Pyrexia | 1 (0.8%)
GENERAL DISORDERS AND ADMINISTRATION SITE CONDITIONS | Infusion site inflammation | 2 (1.6%)

HEMOFIL M was administered to 11 patients previously untreated with Antihemophilic Factor (Human). They have shown no signs of hepatitis or HIV infection following three to nine months of evaluation.

A study of 25 patients treated with HEMOFIL M and monitored for three to six months has demonstrated no evidence of antibody response to mouse protein. More than 1,000 infusions of HEMOFIL M have been administered during the clinical trials. Reported events included a single episode each of chest tightness, fuzziness and dizziness, and one patient reported an unusual taste after each infusion.

Post-marketing Adverse Reactions

In addition to clinical trials, the following adverse reactions have been reported in the post-marketing experience, listed by MedDRA System Organ Class (SOC), then by Preferred Term.

Immune System Disorders: anaphylactic reaction, hypersensitivity

Eye Disorders: visual impairment, ocular hyperemia

Cardiac Disorders: cyanosis, bradycardia, tachycardia

Vascular Disorders: hypotension, flushing

Respiratory, Thoracic, and Mediastinal Disorders: bronchospasm, dyspnea, cough, hyperventilation

Gastrointestinal Disorders: diarrhea, vomiting, nausea, abdominal pain

Skin and Subcutaneous Tissue Disorders: urticaria, rash, pruritus, hyperhidrosis

Musculoskeletal and Connective Tissue Disorders: musculoskeletal pain

General Disorders and Administration Site Conditions: facial edema, edema, chills, fatigue, chest pain, irritability

DOSAGE AND ADMINISTRATION

For intravenous use only.

The expected in vivo peak AHF level, expressed as IU/dL of plasma or % (percent) of normal, can be calculated by multiplying the dose administered per kg body weight (IU/kg) by two. This calculation is based on the clinical finding by Abildgaard, et al,^2 which is supported by data from the collaborative study of in vivo recovery and survival with 15 different lots of HEMOFIL M on 56 hemophiliacs that demonstrated a mean peak recovery point above the mean pre-infusion baseline of about 2.0 IU/dL per infused IU/kg body weight.^3

Examples:

(1) A dose of 1750 IU AHF administered to a 70 kg patient, i.e., 25 IU/kg (1750/70), should be expected to cause a peak post-infusion AHF increase of 25 x 2 = 50 IU/dL (50% of normal).
(2) A peak level of 70% is required in a 40 kg child. In this situation the dose would be 70/2 x 40 = 1400 IU.

Recommended Dosage Schedule

Physician supervision of the dosage is required. The following dosage schedule may be used as a guide.

HEMORRHAGE
Degree of hemorrhage | Required peak post-infusion AHF activity in the blood (as % of normal or IU/dL plasma) | Frequency of infusion
Early hemarthrosis or muscle bleed or oral bleed | 20-40 | Begin infusion every 12 to 24 hours for one-three days until the bleeding episode as indicated by pain is resolved or healing is achieved.
More extensive hemarthrosis, muscle bleed, or hematoma | 30-60 | Repeat infusion every 12 to 24 hours for usually three days or more until pain and disability are resolved.
Life threatening bleeds such as head injury, throat bleed, severe abdominal pain | 60-100 | Repeat infusion every 8 to 24 hours until threat is resolved.
SURGERY
Type of operation
Minor surgery, including tooth extraction | 60-80 | A single infusion plus oral antifibrinolytic therapy within one hour is sufficient in approximately 70% of cases.
Major surgery | 80-100; (pre- and post-operative) | Repeat infusion every 8 to 24 hours depending on state of healing.

If bleeding is not controlled with the prescribed dose, determine the plasma level of Factor VIII and administer a sufficient dose of HEMOFIL M to achieve a satisfactory clinical response.

Under certain circumstances (e.g., presence of a low titer inhibitor) doses larger than those recommended may be necessary as per standard care. In patients with high titer Factor VIII inhibitors, HEMOFIL M therapy may not be effective and other therapeutic options should be considered. The dosage and duration of treatment depend on the severity of Factor VIII deficiency, the location and extent of the bleeding, and the patient's clinical condition. Careful control of replacement therapy is especially important in cases of major surgery or life threatening hemorrhages.

Reconstitution: Use Aseptic Technique

1. Bring HEMOFIL M (dry concentrate) and Sterile Water for Injection, USP, (diluent) to room temperature.
2. Remove caps from concentrate and diluent bottles to expose central portion of rubber stoppers.
3. Cleanse stoppers with germicidal solution.
4. Remove protective covering from one end of double-ended needle and insert exposed needle through diluent stopper.
5. Remove protective covering from other end of double-ended needle. Invert diluent bottle over upright HEMOFIL M bottle, then rapidly insert free end of the needle through the HEMOFIL M bottle stopper at its center. The vacuum in the HEMOFIL M bottle will draw in the diluent.
6. Disconnect the two bottles by removing needle from diluent bottle stopper, then remove needle from HEMOFIL M bottle. Swirl gently until all material is dissolved. Be sure that HEMOFIL M is completely dissolved; otherwise active material will be removed by the filter.

Note: Do not refrigerate after reconstitution.

Administration: Use Aseptic Technique

- Intravenous administration only.
- Administer at room temperature not more than 3 hours after reconstitution.
- Record the name and batch number of the product in order to maintain a link between the patient and the batch of the product.

Intravenous Syringe Injection

- Visually inspect parenteral product for particulate matter and discoloration prior to administration. The solution should be colorless in appearance. Do not administer if particulate matter or discoloration is found.
- Plastic syringes are recommended for use with this product. The ground glass surface of all-glass syringes tend to stick with solutions of this type.
1. Attach filter needle to a disposable syringe and draw back plunger to admit air into syringe.
2. Insert needle into reconstituted HEMOFIL M.
3. Inject air into bottle and then withdraw the reconstituted material into the syringe.
4. Remove and discard the filter needle from the syringe; attach a suitable needle and inject intravenously as instructed under Rate of Administration.
5. If a patient is to receive more than one bottle of HEMOFIL M, the contents of two bottles may be drawn into the same syringe by drawing up each bottle through a separate unused filter needle. This practice lessens the loss of HEMOFIL M. Filter needles are intended to filter the contents of a single bottle of HEMOFIL M only.

Rate of Administration

Administer HEMOFIL M at a rate of up to 10 mL per minute. Infuse HEMOFIL M at a rate of administration that ensures the comfort of the patient [see Precautions: Increase of Pulse Rate].

HOW SUPPLIED

HEMOFIL M is available as single-dose bottles that contain the following nominal potencies:

Nominal Potency | Kit NDC Number
250 IU | 0944-3940-02
500 IU | 0944-3942-02
1000 IU | 0944-3944-02
1700 IU | 0944-3946-02

Each bottle is labeled with the potency in International Units, and is packaged together with 10 mL of Sterile Water for Injection, USP, a double-ended needle, and a filter needle.

Not made with natural rubber latex.

Storage

HEMOFIL M can be stored at 2°C to 8°C (36°F to 46°F) or at room temperature, not to exceed 30°C (86°F), until expiration date noted on the package.

Do not freeze.

Information for Patients

- Advise patients to report any adverse reactions or problems following HEMOFIL M administration to their physician or healthcare provider.
- Advise pregnant women or immune compromised individuals of the effects of Parvovirus B19. Symptoms include fever, drowsiness, chills, runny nose followed about two weeks later by a rash, and joint pain.
- Inform patients of the signs and symptoms of hepatitis A, which include several days to weeks of poor appetite, tiredness, and low-grade fever followed by nausea, vomiting, and pain in the belly. Dark urine and a yellowed complexion are also common symptoms. Encourage patients to consult their physician if such symptoms appear.
- Inform patients of the early signs of hypersensitivity reactions including hives, generalized urticaria, facial edema, flushing, nausea, tightness of the chest, wheezing, dyspnea, hypotension, and anaphylaxis. Advise patients to discontinue use of the product and contact their physician if these symptoms occur.

REFERENCES

1. Horowitz B, Wiebe ME, Lippin A, et al: Inactivation of viruses in labile blood derivatives: 1. Disruption of lipid enveloped viruses by tri(n-butyl)phosphate detergent combinations. Transfusion 25:516-522, 1985.
2. Abildgaard CF, Simone JV, Corrigan JJ, et al: Treatment of hemophilia with glycine-precipitated Factor VIII. New Eng J Med 275:471-475, 1966.
3. Addiego, Jr. JE, Gomperts E, Liu S. et al: Treatment of hemophilia A with a highly purified Factor VIII concentrate prepared by Anti-FVIIIc immunoaffinity chromatography. Thrombosis and Haemostasis 67:19-27, 1992.

To enroll in the confidential, industry-wide Patient Notification System, call 1-888-873-2838.

Takeda Pharmaceuticals U.S.A., Inc.
Cambridge, MA 02142
U.S. License No. 1898

HEMOFIL is a registered trademark of Baxalta Incorporated.
Takeda and are registered trademarks of Takeda Pharmaceutical Company Limited.
©2025 Takeda Pharmaceutical Company Limited. All rights reserved.

Revised: 2/2025

PRINCIPAL DISPLAY PANEL - 10 mL Bottle Label - 250 iU

10 mL size, dried
List 1502845
NDC 0944-3941-01

Antihemophilic Factor (Human)
Method M, Monoclonal Purified
HEMOFIL® M
Nanofiltered

FVIII

Intravenous administration only

Store at 2° - 8°C (36° - 46°F) or room temperature,
not to exceed 30°C (86°F) until expiration date
noted on package.

Dosage and Administration: read package insert.
Contains no preservative.

Rx Only

Takeda Pharmaceuticals U.S.A., Inc.
Cambridge, MA 02142
U.S. License No. 1898

Takeda

PRINCIPAL DISPLAY PANEL - Kit Carton - 250 iU

10 mL size, dried

NDC 0944-3940-02

Antihemophilic Factor (Human)
Method M, Monoclonal Purified
HEMOFIL® M
Nanofiltered

FVIII

Intravenous administration only.

Administer within 3 hours after reconstitution.

Dosage and Administration: Read full prescribing information.

Warning: This product is prepared from large pools of human plasma. Human blood and
its components may transmit infectious agents. The patient and the physician
should discuss the risks and benefits of this product.

Contains no preservative.

Rx Only

Takeda

PRINCIPAL DISPLAY PANEL - 10 mL Bottle Label - 500 iU

10 mL size, dried
List 1502846
NDC 0944-3943-01

Antihemophilic Factor (Human)
Method M, Monoclonal Purified
HEMOFIL® M
Nanofiltered

FVIII

Intravenous administration only

Store at 2° - 8°C (36° - 46°F) or room
temperature, not to exceed 30°C (86°F) until
expiration date noted on package.

Dosage and Administration: read package insert.
Contains no preservative.

Rx Only

Takeda Pharmaceuticals U.S.A., Inc.
Cambridge, MA 02142
U.S. License No. 1898

Takeda

PRINCIPAL DISPLAY PANEL - Kit Carton - 500 iU

10 mL size, dried

NDC 0944-3942-02

Antihemophilic Factor (Human)
Method M, Monoclonal Purified
HEMOFIL® M
Nanofiltered

FVIII

Intravenous administration only.

Administer within 3 hours after reconstitution.

Dosage and Administration: Read full prescribing information.

Warning: This product is prepared from large pools of human plasma. Human blood and
its components may transmit infectious agents. The patient and the physician
should discuss the risks and benefits of this product.

Contains no preservative.

Rx Only

Takeda

PRINCIPAL DISPLAY PANEL - 10 mL Bottle Label - 1000 iU

10 mL size, dried
List 1502847
NDC 0944-3945-01

Antihemophilic Factor (Human)
Method M, Monoclonal Purified
HEMOFIL® M
Nanofiltered

FVIII

Intravenous administration only

Store at 2° - 8°C (36° - 46°F) or room temperature,
not to exceed 30°C (86°F) until expiration date noted
on package.

Dosage and Administration: read package insert.
Contains no preservative.

Rx Only

Takeda Pharmaceuticals U.S.A., Inc.
Cambridge, MA 02142
U.S. License No. 1898

Takeda

PRINCIPAL DISPLAY PANEL - Kit Carton - 1000 iU

10 mL size, dried

NDC 0944-3944-02

Antihemophilic Factor (Human)
Method M, Monoclonal Purified
HEMOFIL® M
Nanofiltered

FVIII

Intravenous administration only.

Administer within 3 hours after reconstitution.

Dosage and Administration: Read full prescribing information.

Warning: This product is prepared from large pools of human plasma. Human blood and
its components may transmit infectious agents. The patient and the physician
should discuss the risks and benefits of this product.

Contains no preservative.

Rx Only

Takeda

PRINCIPAL DISPLAY PANEL - 10 mL Bottle Label - 1700 iU

10 mL size, dried
List 1502848
NDC 0944-3947-01

Antihemophilic Factor (Human)
Method M, Monoclonal Purified
HEMOFIL® M
Nanofiltered

FVIII

Intravenous administration only

Store at 2° - 8°C (36° - 46°F) or room
temperature, not to exceed 30°C (86°F) until
expiration date noted on package.

Dosage and Administration: read package insert.
Contains no preservative.

Rx Only

Takeda Pharmaceuticals U.S.A., Inc.
Cambridge, MA 02142
U.S. License No. 1898

Takeda

PRINCIPAL DISPLAY PANEL - Kit Carton - 1700 iU

10 mL size, dried

NDC 0944-3946-02

Antihemophilic Factor (Human)
Method M, Monoclonal Purified
HEMOFIL® M
Nanofiltered

FVIII

Intravenous administration only.

Administer within 3 hours after reconstitution.

Dosage and Administration: Read full prescribing information.

Warning: This product is prepared from large pools of human plasma. Human blood and
its components may transmit infectious agents. The patient and the physician
should discuss the risks and benefits of this product.

Contains no preservative.

Rx Only

Takeda

PRINCIPAL DISPLAY PANEL - 10 mL Vial Label

10 mL

NDC 64764-516-10

Takeda

Sterile Water for Injection, USP
for reconstitution of accompanying product

Do not use unless clear. No antimicrobial agent or other substance
has been added. Do not use for intravascular injection without making
approximately isotonic by addition of suitable solute.
Discard unused portion. Rx Only

Single-dose container
Nonpyrogenic

6521215